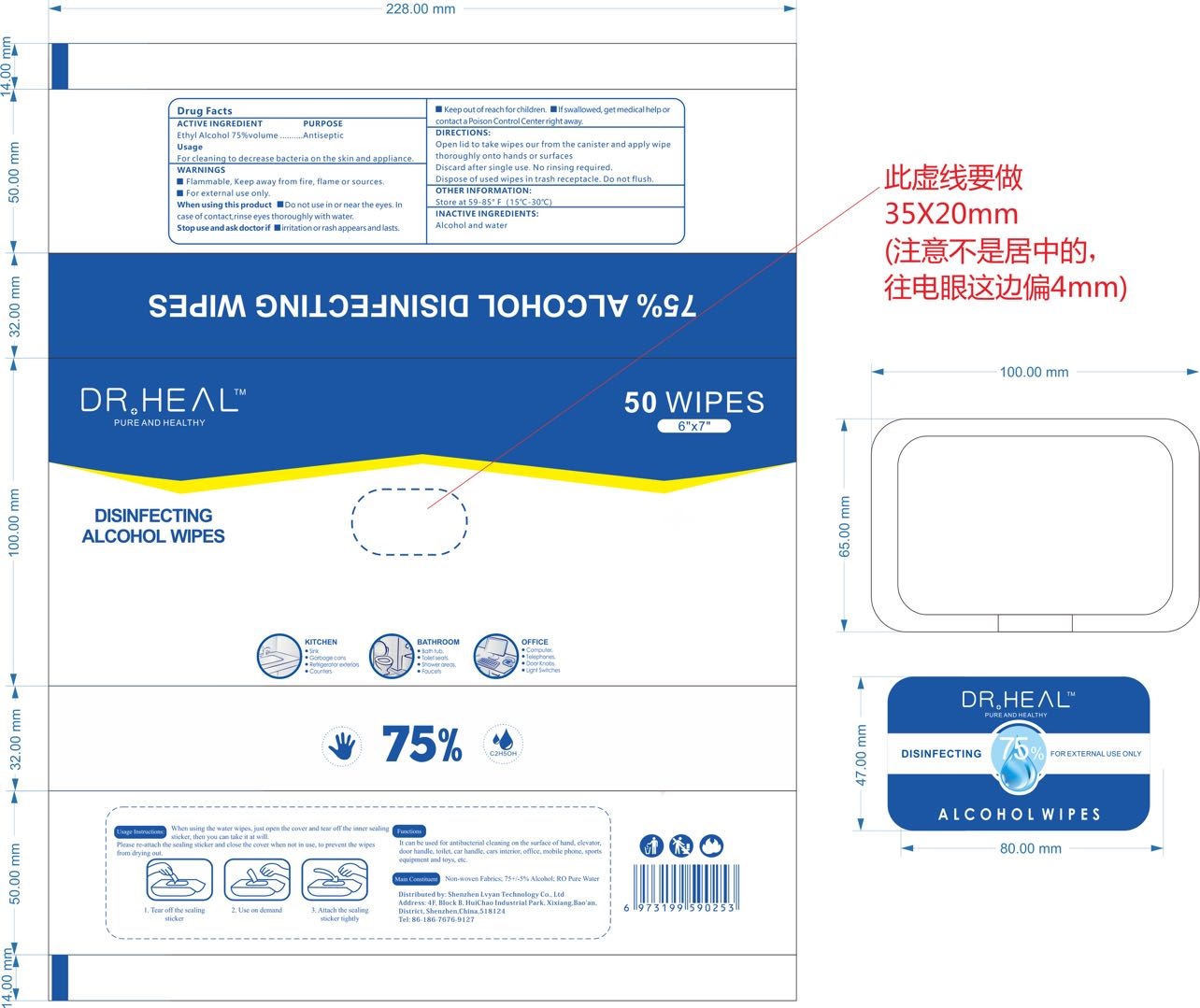 DRUG LABEL: DR.HEAL Disinfecting Alcohol Wipes
NDC: 78031-201 | Form: CLOTH
Manufacturer: Shenzhen Lvyan Technology Co., Ltd.
Category: otc | Type: HUMAN OTC DRUG LABEL
Date: 20200612

ACTIVE INGREDIENTS: ALCOHOL 2.02 g/1 1
INACTIVE INGREDIENTS: WATER

DR.HEAL Disinfecting Alcohol Wipes

DR.HEAL Disinfecting Alcohol Wipes

Active Ingredient(s)

ALCOHOL 2.4g/pcs. Purpose: Antiseptic

Purpose

Antiseptic, DR.HEAL Disinfecting Alcohol Wipes

Use

DR.HEAL Disinfecting Alcohol Wipes to help reduce bacteria that potentially can cause disease. For use when soap and water are not available.

Warnings

For external use only. Flammable. Keep away from heat or flame

Do not use

- in children less than 2 months of age
- on open skin wounds

When using this product keep out of eyes, ears, and mouth. In case of contact with eyes, rinse eyes thoroughly with water.
Stop use and ask a doctor if irritation or rash occurs. These may be signs of a serious condition.
Keep out of reach of children. If swallowed, get medical help or contact a Poison Control Center right away.

Stop use and ask a doctor if irritation or rash occurs. These may be signs of a serious condition.

Keep out of reach of children. If swallowed, get medical help or contact a Poison Control Center right away.

Directions

- Open lid to take wipes our from the canister and apply wipe thoroughly onto hands or surfaces.
- Discard after single use. No rinsing required.
- Dispose of used wipes in trash receptacle. Do not flsuh.
- Supervise children under 6 years of age when using this product to avoid swallowing.

Other information

- Store between 15-30C (59-86F)
- Avoid freezing and excessive heat above 40C (104F)

Inactive ingredients

purified water USP